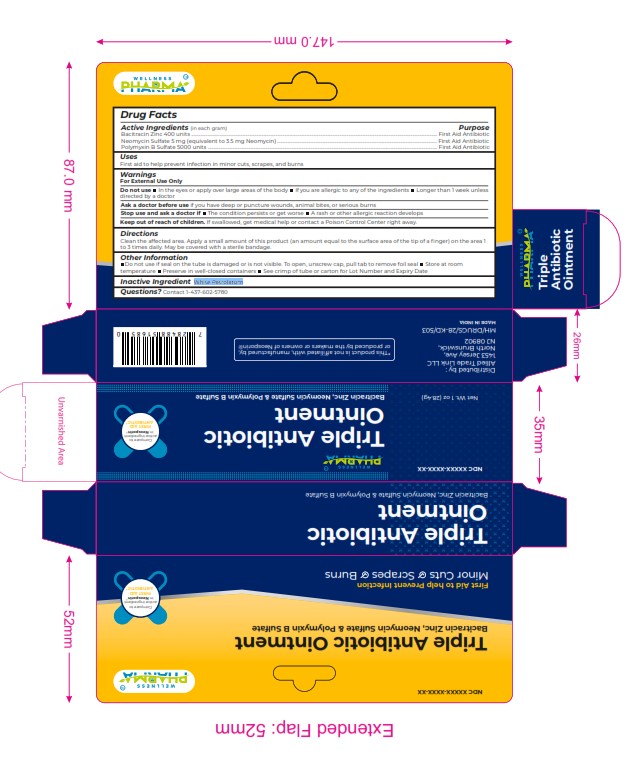 DRUG LABEL: TRIPLET ANTIBIOTIC
NDC: 84387-006 | Form: OINTMENT
Manufacturer: ALLIED TRADE LINK LLC
Category: otc | Type: HUMAN OTC DRUG LABEL
Date: 20241112

ACTIVE INGREDIENTS: BACITRACIN ZINC 400 [USP'U]/1 g; NEOMYCIN SULFATE 5 mg/1 g; POLYMYXIN B SULFATE 5000 [iU]/1 g
INACTIVE INGREDIENTS: WHITE PETROLATUM

TRIPLE ANTIBIOTIC

DOSAGE AND ADMINISTRATION

Active Ingredients (in each gram) Purpose
Bacitracin Zinc 400 units ................................................................................................................................................................................................................... First Aid Antibiotic
Neomycin Sulfate 5 mg (equivalent to 3.5 mg Neomycin) ......................................................................................................................................... First Aid Antibiotic
Polymyxin B Sulfate 5000 units ..................................................................................................................................................................................................... First Aid Antibiotic

WARNINGS

For External Use Only
Do not use In the eyes or apply over large areas of the body If you are allergic to any of the ingredients Longer than 1 w eek unless
directed by a doctor
Ask a doctor before use if you have deep or puncture wounds, animal bites, or serious burns
Stop use and ask a doctor if The condition persists or get worse A rash or other allergic reaction develops
Keep out of reach of children. If swallowed, get medical help or contact a Poison Control Center right away.

Inactive Ingredient White Petrolatum

INDICATIONS AND USAGE

Clean the affected area. Apply a small amount of this product (an amount equal to the surface area of the tip of a ﬁnger) on the area 1
to 3 times daily. May be covered with a sterile bandage.

Keep out of reach of children. If swallowed, get medical help or contact a Poison Control Center right away.

PURPOSE

... First Aid Antibiotic